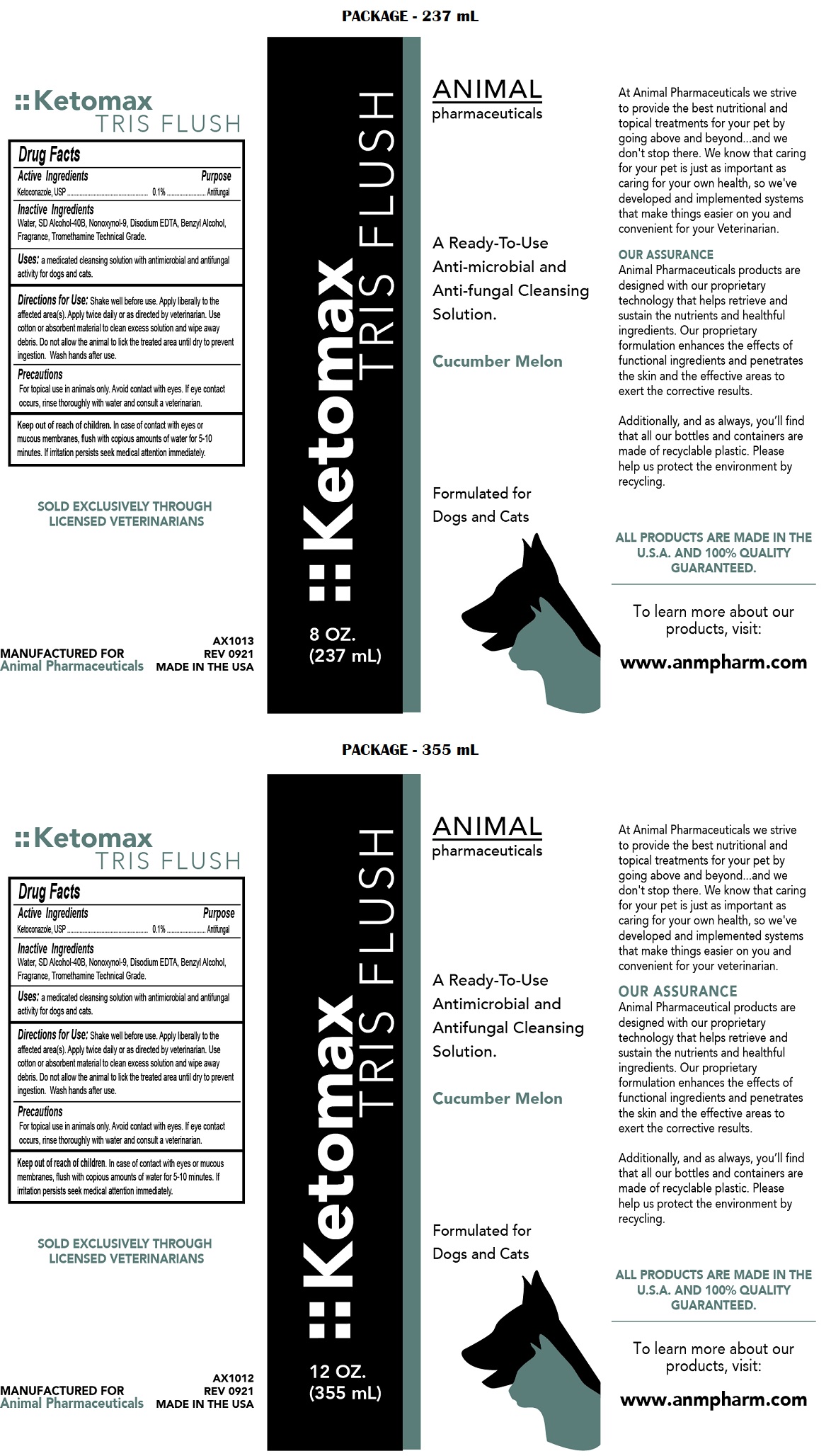 DRUG LABEL: Ketomax TRIS FLUSH
NDC: 68898-120 | Form: SOLUTION
Manufacturer: Animal Pharmaceuticals
Category: animal | Type: OTC ANIMAL DRUG LABEL
Date: 20221121

ACTIVE INGREDIENTS: KETOCONAZOLE 0.1 g/100 mL
INACTIVE INGREDIENTS: WATER; ALCOHOL; NONOXYNOL-9; EDETATE DISODIUM ANHYDROUS; BENZYL ALCOHOL; TROMETHAMINE

Ketomax TRIS FLUSH

Active Ingredients

Ketoconazole, USP 0.1%

Purpose

Antifungal

Inactive Ingredients

Water, SD Alcohol-40B, Nonoxynol-9, Disodium EDTA, Benzyl Alcohol, Fragrance, Tromethamine Technical Grade.

Uses:

a medicated cleansing solution with antimicrobial and antifungal activity for dogs and cats.

Directions for Use:

Shake well before use. Apply liberally to the affected area(s). Apply twice daily or as directed by veterinarian. Use cotton or absorbent material to clean excess solution and wipe away debris. Do not allow the animal to lick the treated area until dry to prevent ingestion. Wash hands after use.

Precautions

For topical use in animals only. Avoid contact with eyes. If eye contact occurs, rinse thoroughly with water and consult a veterinarian.

Keep out of reach of children. In case of contact with eyes or mucous membranes, flush with copious amounts of water for 5-10 minutes. If irritation persists seek medical attention immediately.

A Ready-To-Use Antimicrobial and Antifungal Cleansing Solution.

Formulated for Dogs and Cats

At Animal Pharmaceuticals we strive to provide the best nutritional and topical treatments for your pet by going above and beyond....and we don't stop there. We know that caring for your pet is just as important as caring for your own health, so we've developed and implemented systems that make things easier on you and convenient for your Veterinarian.

OUR ASSURANCE
Animal Pharmaceuticals products are designed with our proprietary technology that helps retrieve and sustain the nutrients and healthful ingredients. Our proprietary formulation enhances the effects of functional ingredients and penetrates the skin and the effective areas to exert the corrective results.

Additionally, and as always, you'll find that all our bottles and containers are made of recyclable plastic. Please help us protect the environment by recycling.

ALL PRODUCTS ARE MADE IN THE U.S.A. AND 100% QUALITY GUARANTEED.

To learn more about our products, visit:

www.anmpharm.com

SOLD EXCLUSIVELY THROUGH LICENSED VETERINARIANS

MANUFACTURED FOR
Animal Pharmaceuticals

MADE IN THE USA